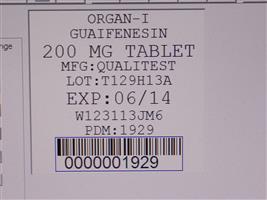 DRUG LABEL: ORGAN-I NR
NDC: 68151-1929 | Form: TABLET
Manufacturer: Carilion Materials Management
Category: otc | Type: HUMAN OTC DRUG LABEL
Date: 20171228

ACTIVE INGREDIENTS: GUAIFENESIN 200 mg/1 1
INACTIVE INGREDIENTS: D&C RED NO. 30; MAGNESIUM STEARATE; MALTODEXTRIN; MICROCRYSTALLINE CELLULOSE; STARCH, CORN; SILICON DIOXIDE; STEARIC ACID

ORGAN-I NR

Active ingredient

Guaifenesin, USP 200 mg

Purpose

Expectorant

Use

helps loosen phlegm (mucus) and thin bronchial secretions to make coughs more productive

Ask a doctor before use if you have

- cough that occurs with too much phlegm (mucus)
- cough that lasts or is chronic such as occurs with smoking, asthma, chronic bronchitis, or emphysema

STOP USE

cough lasts more than 7 days, comes back or is accompanied by fever, rash, or persistent headache. These could be signs of a serious condition. Stop use and ask a doctor if

PREGNANCY OR BREAST FEEDING

ask a health professional before use. If pregnant or breast-feeding,

Keep out of reach of children.

In case of overdose, get medical help or contact a Poison Control Center right away.

Directions

- do not take more than 6 doses in any 24-hour period
- this adult product is not intended for use in children under 12 years of age

adults and children 12 years and over | 1 - 2 tablets every 4 hours
children under 12 years | do not use

Other information

- store at 15° to 30°C (59° to 86°F)

You may report serious side effects to: . 130 Vintage Drive, Huntsville, AL 35811

Inactive ingredients

D&C red #30 aluminum lake, magnesium stearate, maltodextrin, microcrystalline cellulose, polyvinylpyrrolidine, pregelatinized starch, silicon dioxide, stearic acid

Made in the for Qualitest Pharmaceuticals Huntsville, AL 35811 USA

Rev. 3/11 R5 8080143 4740

HOW SUPPLIED

Product: 68151-1929

NDC: 68151-1929-2 1 TABLET in a PACKAGE